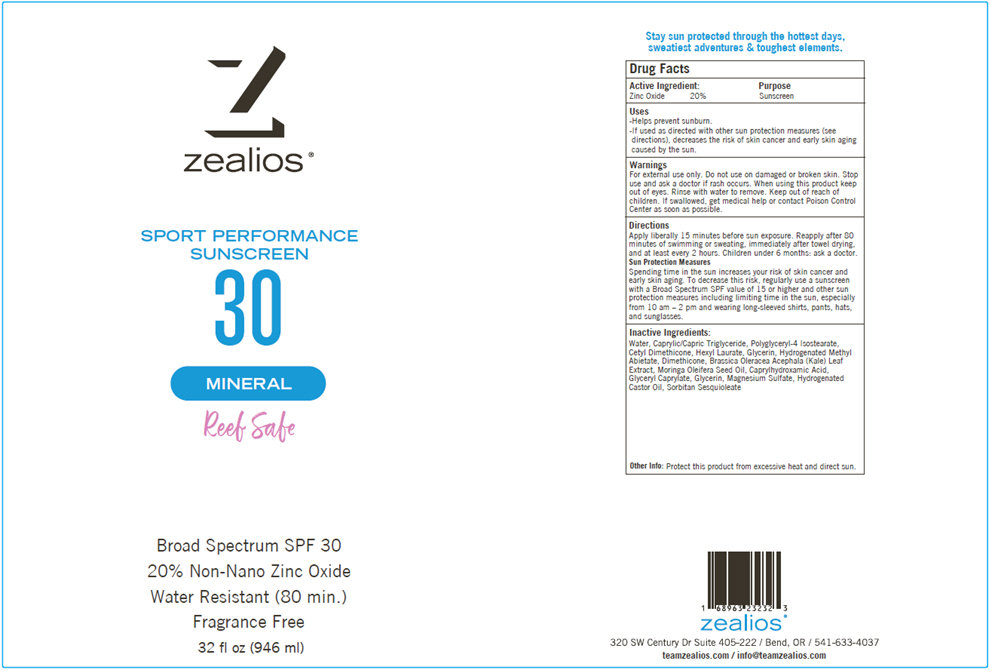 DRUG LABEL: Zealios Mineral SPF 30 Sunscreen
NDC: 83326-004 | Form: CREAM
Manufacturer: Personal Best Products Inc. dba Zealios
Category: otc | Type: HUMAN OTC DRUG LABEL
Date: 20260203

ACTIVE INGREDIENTS: ZINC OXIDE 17600 mg/1 1
INACTIVE INGREDIENTS: Water; Medium-Chain Triglycerides; Polyglyceryl-4 Isostearate; Hexyl Laurate; Glycerin; Hydrogenated Methyl Abietate; Dimethicone, Unspecified; Caprylhydroxamic Acid; Glyceryl Monocaprylate; Magnesium Sulfate, Unspecified Form; Hydrogenated Castor Oil; Sorbitan Sesquioleate; Kale; Moringa Oleifera Seed Oil

Zealios® Mineral SPF 30 Sunscreen

Drug Facts

Active Ingredient

Zinc Oxide 20%

Purpose

Sunscreen

Uses

- Helps prevent sunburn.
- If used as directed with other sun protection measures (see directions), decreases the risk of skin cancer and early skin aging caused by the sun.

Warnings

For external use only. Do not use on damaged or broken skin. Stop use and ask a doctor if rash occurs. When using this product keep out of eyes. Rinse with water to remove.

Keep out of reach of children. If swallowed, get medical help or contact Poison Control Center as soon as possible.

Directions

Apply liberally 15 minutes before sun exposure. Reapply after 80 minutes of swimming or sweating, immediately after towel drying, and at least every 2 hours. Children under 6 months: ask a doctor.

Sun Protection Measures

Spending time in the sun increases your risk of skin cancer and early skin aging. To decrease this risk, regularly use a sunscreen with a Broad Spectrum SPF value of 15 or higher and other sun protection measures including limiting time in the sun, especially from 10 am – 2 pm and wearing long-sleeved shirts, pants, hats, and sunglasses.

Inactive Ingredients

Water, Caprylic/Capric Triglyceride, Polyglyceryl-4 Isostearate, Cetyl Dimethicone, Hexyl Laurate, Glycerin, Hydrogenated Methyl Abietate, Dimethicone, Brassica Oleracea Acephala (Kale) Leaf Extract, Moringa Oleifera Seed Oil, Caprylhydroxamic Acid, Glyceryl Caprylate, Glycerin, Magnesium Sulfate, Hydrogenated Castor Oil, Sorbitan Sesquioleate

Other Info

Protect this product from excessive heat and direct sun.

PRINCIPAL DISPLAY PANEL - 946 ml Bottle Label

zealios®

SPORT PERFORMANCE
SUNSCREEN
30

MINERAL

Reef Safe

Broad Spectrum SPF 30
20% Non-Nano Zinc Oxide
Water Resistant (80 min.)
Fragrance Free

32 fl oz (946 ml)